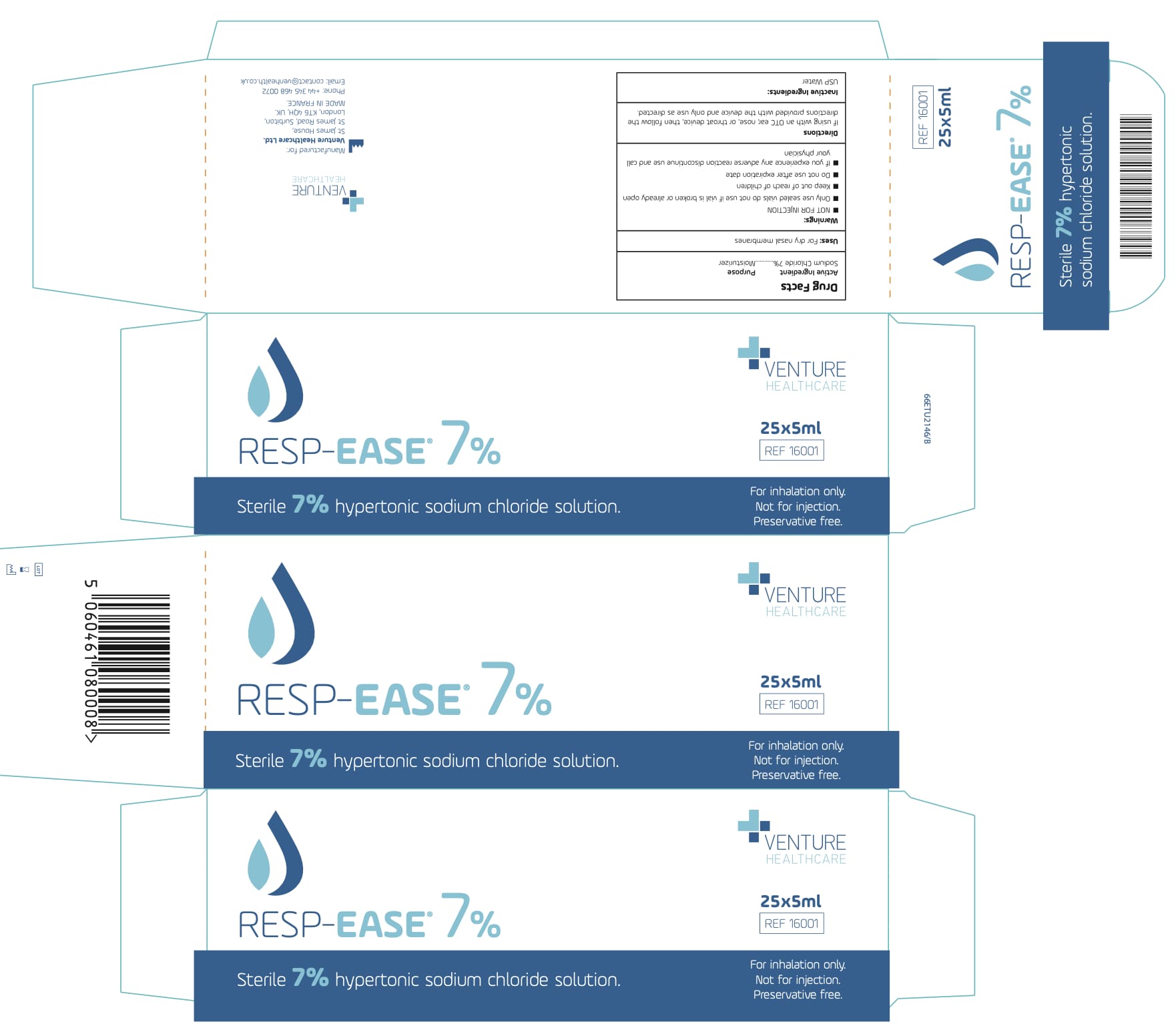 DRUG LABEL: RESP EASE
NDC: 43014-1114 | Form: LIQUID
Manufacturer: Laboratoire Unither
Category: otc | Type: HUMAN OTC DRUG LABEL
Date: 20250401

ACTIVE INGREDIENTS: SODIUM CHLORIDE 70 mg/1 mL
INACTIVE INGREDIENTS: WATER

Unither -Venture Saline Solution 7% Sodium Chloride

Active ingredient

Sodium Chloride 7%

Purpose

Moisturizer

Uses:

For dry nasal membranes

Warnings

NOT FOR INJECTION

Only use sealed vials do not use if vial is broken or already open

Keep out of reach of children
Do not use after expiration date

If you experience any adverse reaction discontinue use and call your physician

• Do not use

after expiration date

- Discontinue if you experience any adverse reaction and call your physician

Directions

If using with an OTC ear, nose, or throat device, then follow the directions provided with the device and only use as directed.

Inactive ingredients

USP Water

Package Labelling:

5 mL NDC: 43014-1114-1